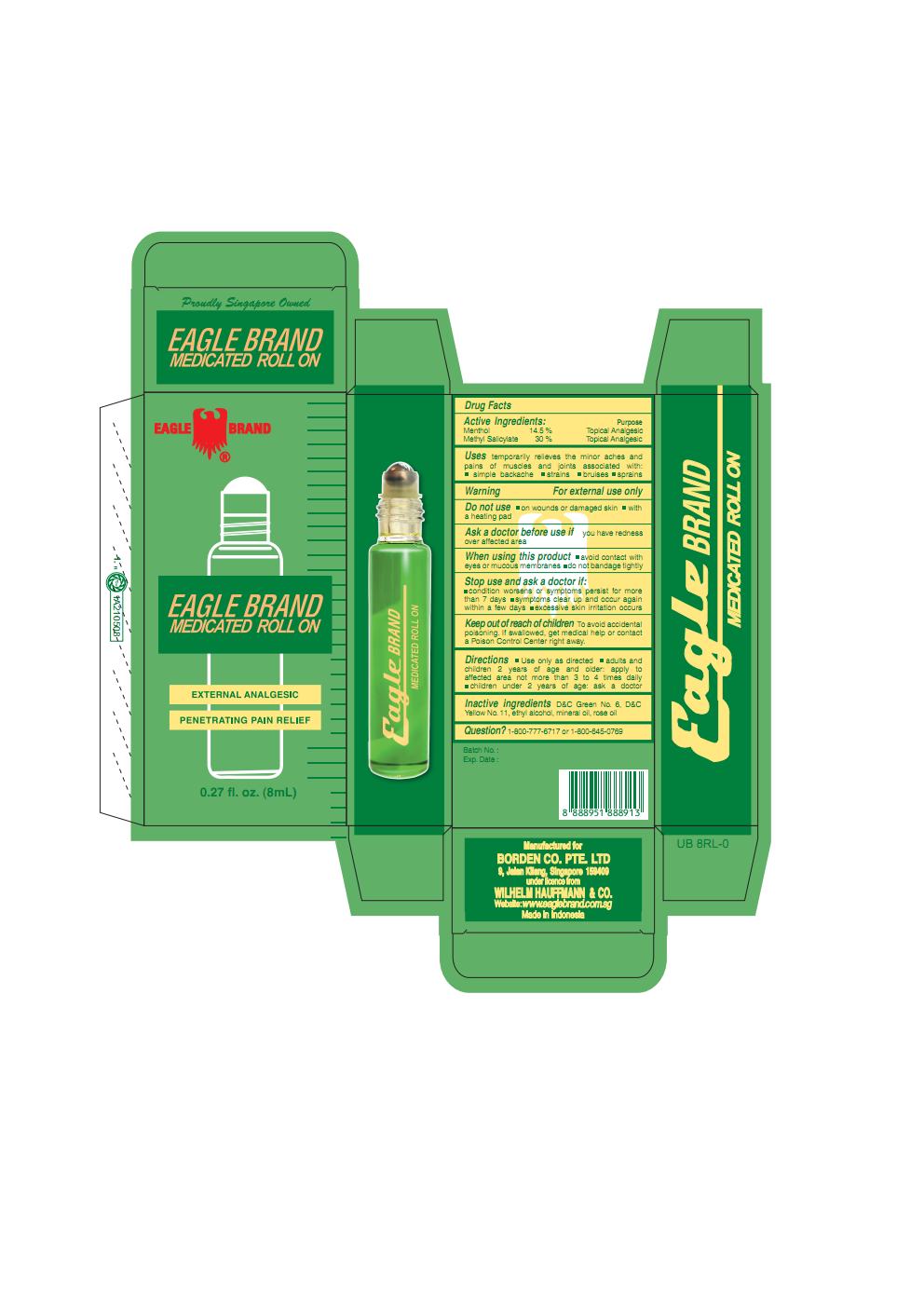 DRUG LABEL: Eagle
NDC: 60954-008 | Form: OIL
Manufacturer: Eagle Indo Pharma
Category: otc | Type: HUMAN OTC DRUG LABEL
Date: 20241007

ACTIVE INGREDIENTS: MENTHOL 14.5 g/100 mL; METHYL SALICYLATE 30 g/100 mL
INACTIVE INGREDIENTS: D&C YELLOW NO. 11; D&C GREEN NO. 6; ALCOHOL; MINERAL OIL; ROSE OIL

Eagle Menthol Mthylslcylte Oil

Active Ingredients

Menthol 14.5%
Methyl Salicylate 30%

Purpose

Topical Analgesic

Topical Analgesic

Uses

temporarily relieves the minor aches and pains of muscle and joints associated with :

■simple backache ■strains ■bruises ■sprains

Warning

For external use only

Do not use

■ on wounds or damaged skin ■ with a heating pad

Ask a doctor before use if

you have redness over affected area

When using this product

■avoid contact with eyes or mucous membranes ■do not bandage tightly

Stop use and ask a doctor if

■condition worsens or symptoms persist for more than 7 days ■symptoms clear up and occur again within a few days ■excessive skin irritation occurs

Keep out of reach of children

Keep out of reach of childrenTo avoid accidental poisoning. If swallowed, get medical help or contact a Poison Control Center right away.

Directions

■ Use only as directed ■adults and children 2 years and over: apply to affected area not more than 3 to 4 time daily ■children under 2 years of age: ask a doctor

Inactive ingredients

D&C Green No. 6, D&C Yellow No. 11, ethyl alcohol, mineral oil, rose oil

Question?

1-800-777-6717 or 1-800-645-0769